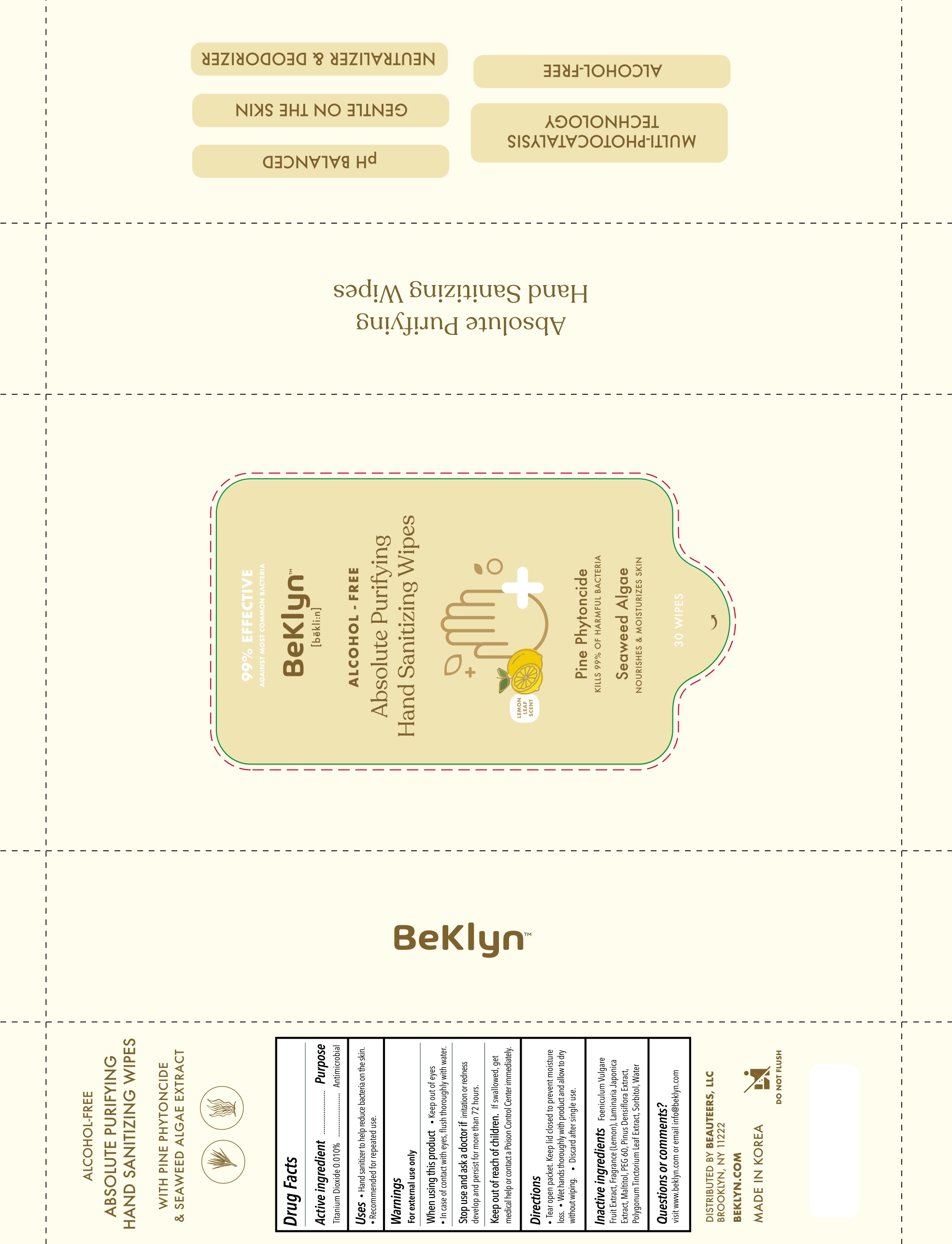 DRUG LABEL: Beklyn Absolute Purifying Hand Sanitizing Wipes
NDC: 71544-0013 | Form: CLOTH
Manufacturer: MY Corp.,Ltd
Category: otc | Type: HUMAN OTC DRUG LABEL
Date: 20200805

ACTIVE INGREDIENTS: TITANIUM DIOXIDE 0.56 g/30 1
INACTIVE INGREDIENTS: WATER; FOENICULUM VULGARE FRUIT; PERSICARIA TINCTORIA LEAF; SORBITOL; MALTITOL; LAMINARIA JAPONICA

MY Corp - Beklyn Absolute Purifying Hand Sanitizing Wipes

ACTIVE INGREDIENT

titanium dioxide

INACTIVE INGREDIENT

Foeniculum Vulgare Fruit Extract, Fragrance - Lemon, Laminaria Japonica Extract, Maltitol, PEG 60, Pinus Densiflora Extract, Polygonum Tinctoric Leaf Extract, Sorbitol, Water

PURPOSE

- Hand Santizer to help reduce bacteria on the skin.
- Recommended for repeated use.

keep out of reach of the children

INDICATIONS AND USAGE

- Tear open packet. Keep lid closed to prevent moisture loss
- Wet hadns throughly with prodict and allow to dry wipping.
- Discard after single use.

WARNINGS

For external use only.

When using this product keep out of eyes, ears, and mouth. In case of contact with eyes, rinse thoroughly with water.

Stop use and ask a doctor if irritation or rash occurs develop and persist for more than 72 hours.

Keep out of reach of children. If swallowed, get medical help or contact a Poison Control Center right away.

DOSAGE AND ADMINISTRATION

for external use only